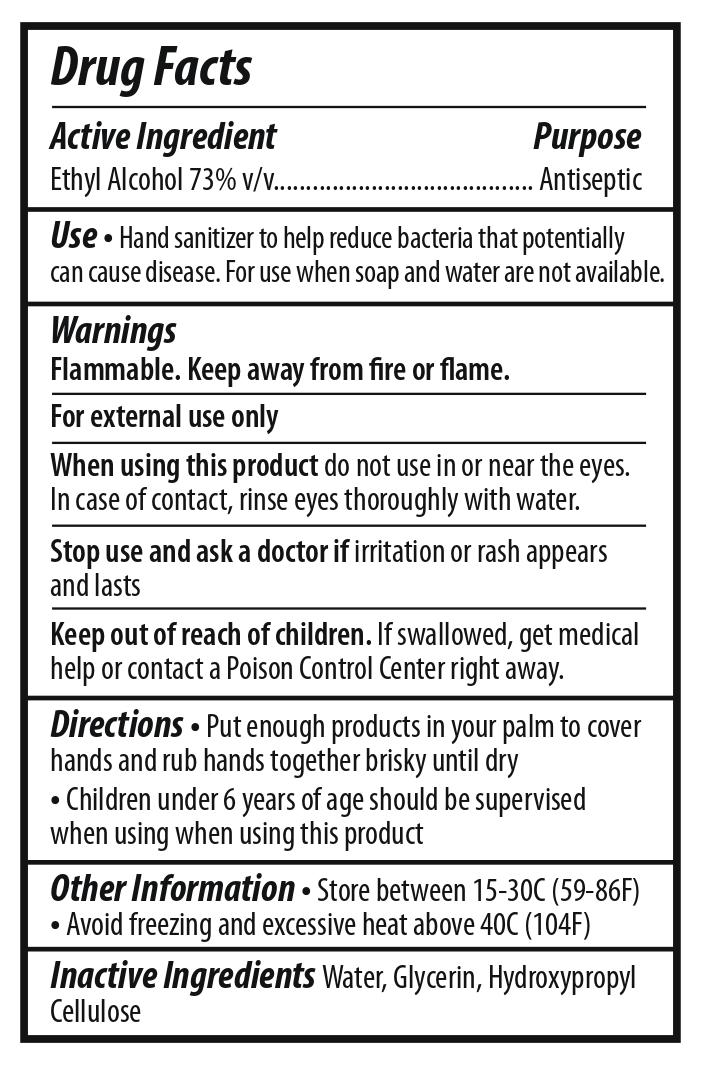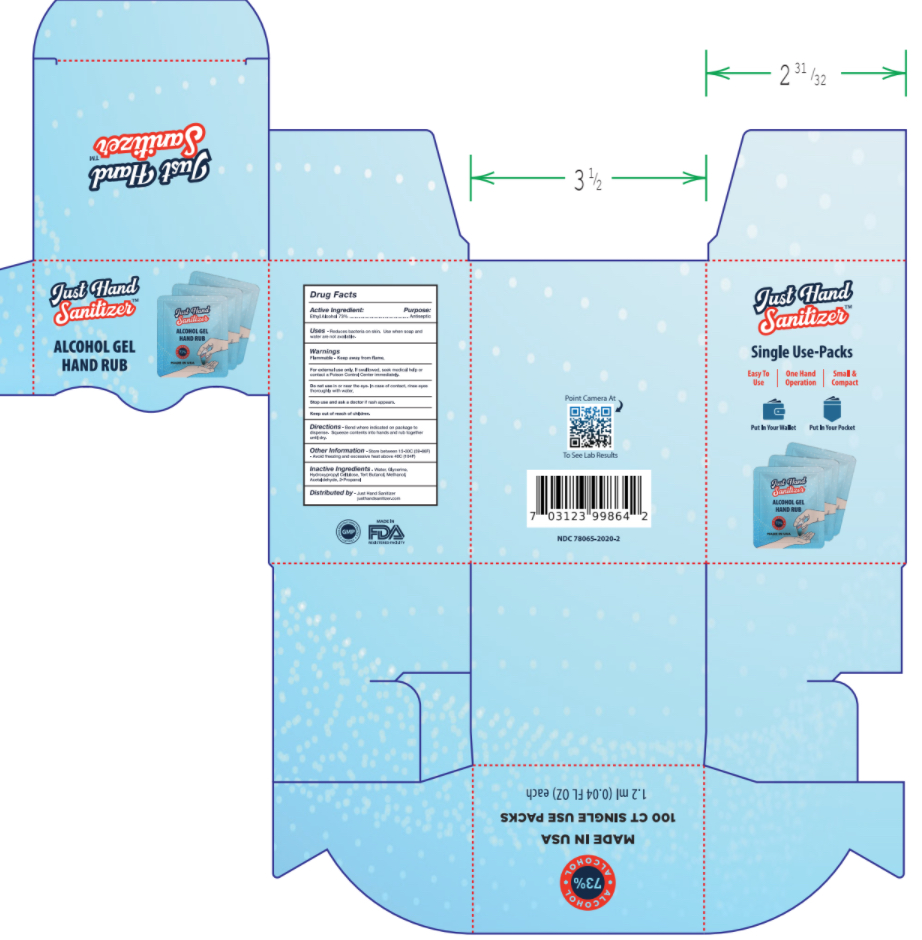 DRUG LABEL: Hand Sanitizer
NDC: 78065-2020 | Form: GEL
Manufacturer: STUDIO 320
Category: otc | Type: HUMAN OTC DRUG LABEL
Date: 20200601

ACTIVE INGREDIENTS: ALCOHOL 0.876 mL/1.2 mL
INACTIVE INGREDIENTS: GLYCERIN 0.03 mL/1.2 mL; HYDROXYPROPYL CELLULOSE, UNSPECIFIED 0.013 mL/1.2 mL; WATER 0.277 mL/1.2 mL

Just Hand Sanitizer

Active Ingredient(s)

Ethyl Alcohol 73%.

Purpose

Antiseptic

Use

Reduces bacteria on skin. Use when soap and water are not available.

Warnings

Flammable. Keep away from flame.

Purpose

For external use only. If swallowed, seek medical help or contact a Poison Control Center immediately.

Keep out of reach of children.

Do not use in or near the eyes. In case of contact, rinse eyes thoroughly with water.

Stop use and ask a doctor if rash appears.

Directions

Bend where indicated on package to dispense. Squeeze contents into hands and rub together until dry.

Other information

- Store between 15-30C (59-86F)
- Avoid freezing and excessive heat above 40C (104F)

Inactive ingredients

Water, Glycerin, Hydroxypropyl Cellulose

Package Label - Principal Display Panel

Just Hand Sanitizer box